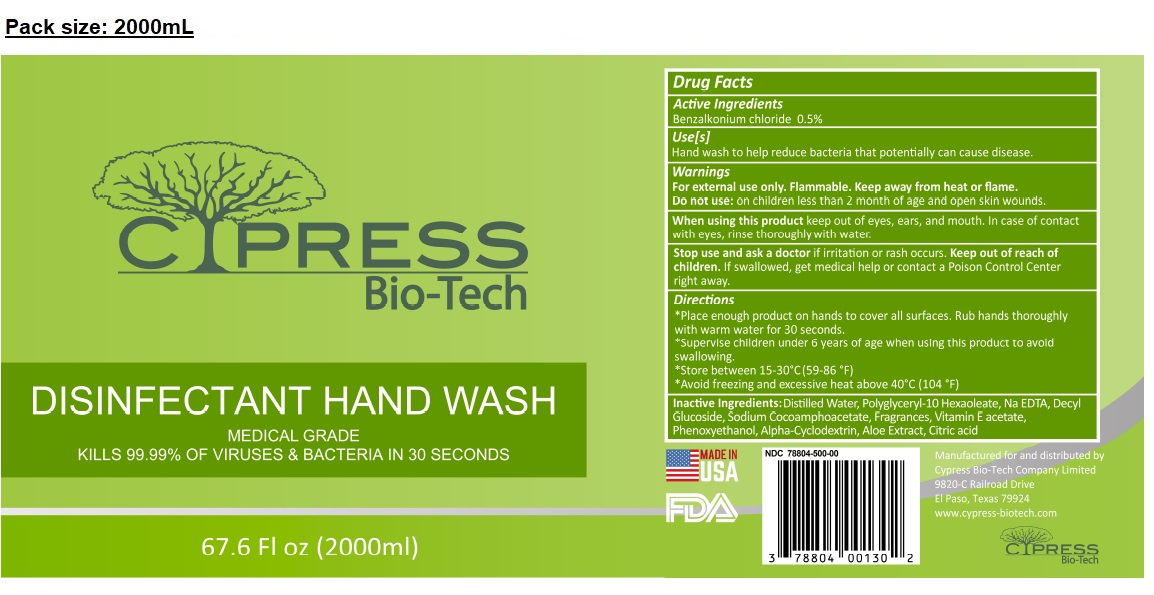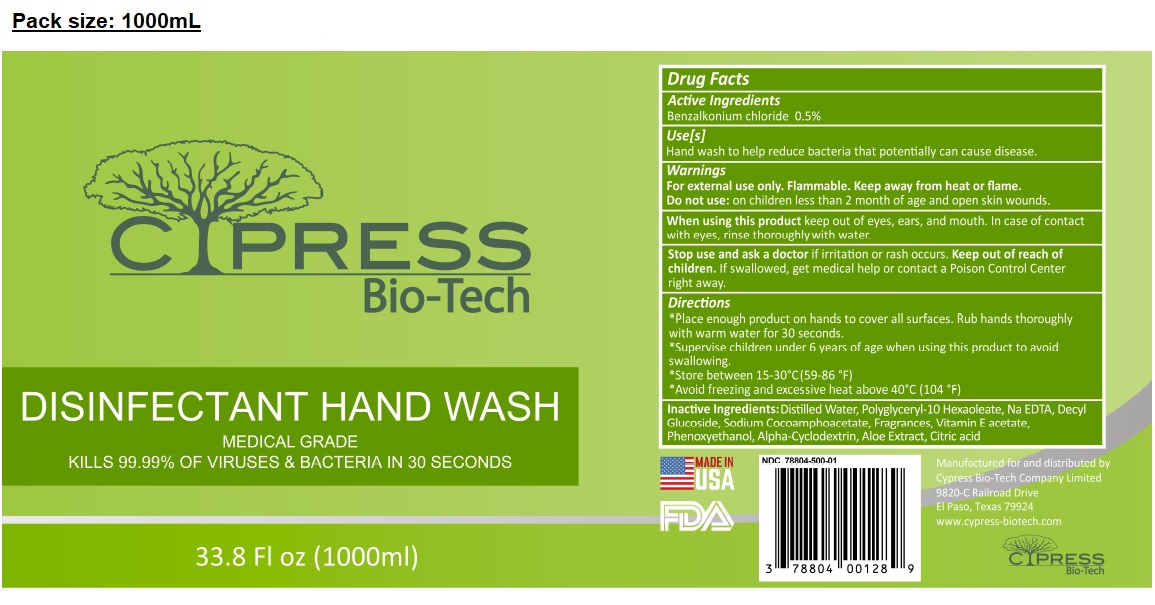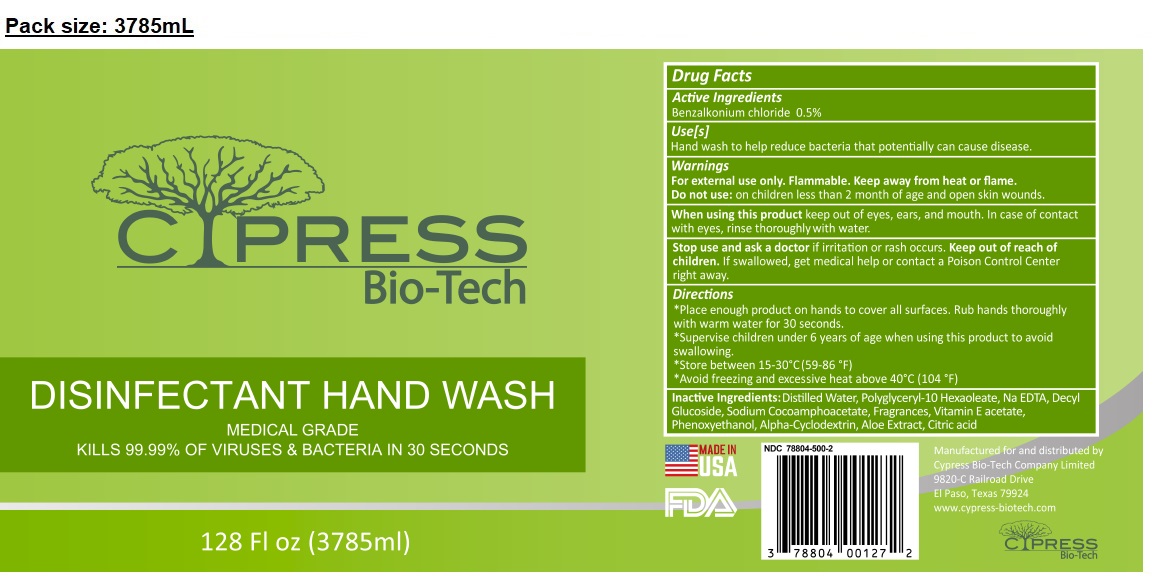 DRUG LABEL: Cypress Bio-Tech Disinfectant Hand Wash
NDC: 78804-500 | Form: LIQUID
Manufacturer: Allure Chemicals LP
Category: otc | Type: HUMAN OTC DRUG LABEL
Date: 20210311

ACTIVE INGREDIENTS: BENZALKONIUM CHLORIDE 0.5 g/100 mL
INACTIVE INGREDIENTS: WATER; POLYGLYCERYL-10 HEXAOLEATE; EDETATE SODIUM; DECYL GLUCOSIDE; SODIUM COCOAMPHOACETATE; .ALPHA.-TOCOPHEROL ACETATE; PHENOXYETHANOL; ALFADEX; ALOE; CITRIC ACID MONOHYDRATE

CYPRESS Bio-Tech DISINFECTANT HAND WASH

Active Ingredients

Benzalkonium chloride 0.5%

Purpose

Antibacterial

Use[s]

Hand wash to help reduce bacteria that potentially can cause disease.

Warnings

For external use only. Flammable. Keep away from heat or flame.

Do not use: on children less than 2 months of age and open skin wounds.

When using this product keep out of eyes, ears, and mouth. In case of contact with eyes, rinse thoroughly with water.

Stop use and ask a doctor if irritation or rash occurs.

Keep out of reach of children. If swallowed, get medical help or contact a Poison Control Center right away.

Directions

*Place enough product on hands to cover all surfaces. Rub hands thoroughly with warm water for 30 seconds.

*Supervise children under 6 years of age when using this product to avoid swallowing.

*Store between 15-30°C (59-86 °F)

*Avoid freezing and excessive heat above 40°C (104 °F)

Inactive Ingredients:

Distilled Water, Polyglyceryl-10 Hexaoleate, Na EDTA, Decyl Glucoside, Sodium Cocoamphoacetate, Fragrances, Vitamin E acetate, Phenoxyethanol, Alpha-Cyclodextrin, Aloe Extract, Citric acid

MEDICAL GRADE

KILLS 99.99% OF VIRUSES & BACTERIA IN 30 SECONDS

Manufactured for and distributed by

Cypress Bio-Tech Company Limited

9820-C Railroad Drive

El Paso, Texas 79924

www.cypress-biotech.com

MADE IN USA